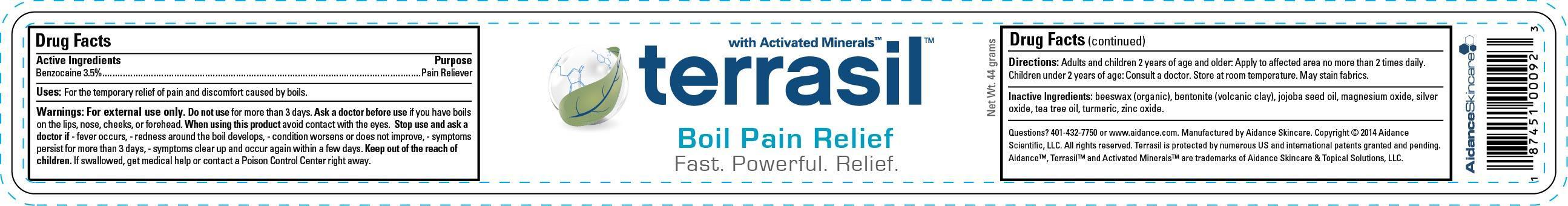 DRUG LABEL: Terrasil Boil Pain Relief
NDC: 24909-120 | Form: OINTMENT
Manufacturer: Aidance Skincare & Topical Solutions, LLC
Category: otc | Type: HUMAN OTC DRUG LABEL
Date: 20140620

ACTIVE INGREDIENTS: BENZOCAINE 3.5 g/100 g
INACTIVE INGREDIENTS: BENTONITE; JOJOBA OIL; MAGNESIUM OXIDE; SILVER OXIDE; TEA TREE OIL; TURMERIC; WHITE WAX; ZINC OXIDE

Drug Facts

Active Ingredient

Benzocaine 3.5%

Purpose

Pain Reliever

Uses

For the temporary relief of pain and discomfort caused by boils.

Warnings

For external use only. Do not use for more than 3 days. Ask a doctor before use if you have boils on the lips, nose, cheeks, or forehead. When using this product avoid contact with the eyes. Stop use and ask a doctor if - fever occurs, - redness around the boil develops, - condition worsens or does not improve, - symptoms persist for more than 3 days, - symptoms clear up and occur again within a few days.

Keep out of reach of children.

If swallowed, get medical help or contact a Poison Control Center right away.

Directions

Adults and children 2 years of age and older: Apply to affected area no more than 2 times daily. Children under 2 years of age: Consult a doctor. Store at room temperature. May stain fabrics.

Inactive Ingredients

beeswax (organic), bentonite (volcanic clay), jojoba seed oil, magnesium oxide, silver oxide, tea tree oil, turmeric, zinc oxide.

PRINCIPAL DISPLAY PANEL - 44g Label

terrasil with Activated Minerals

Boil Pain Relief
Fast. Powerful. Relief.